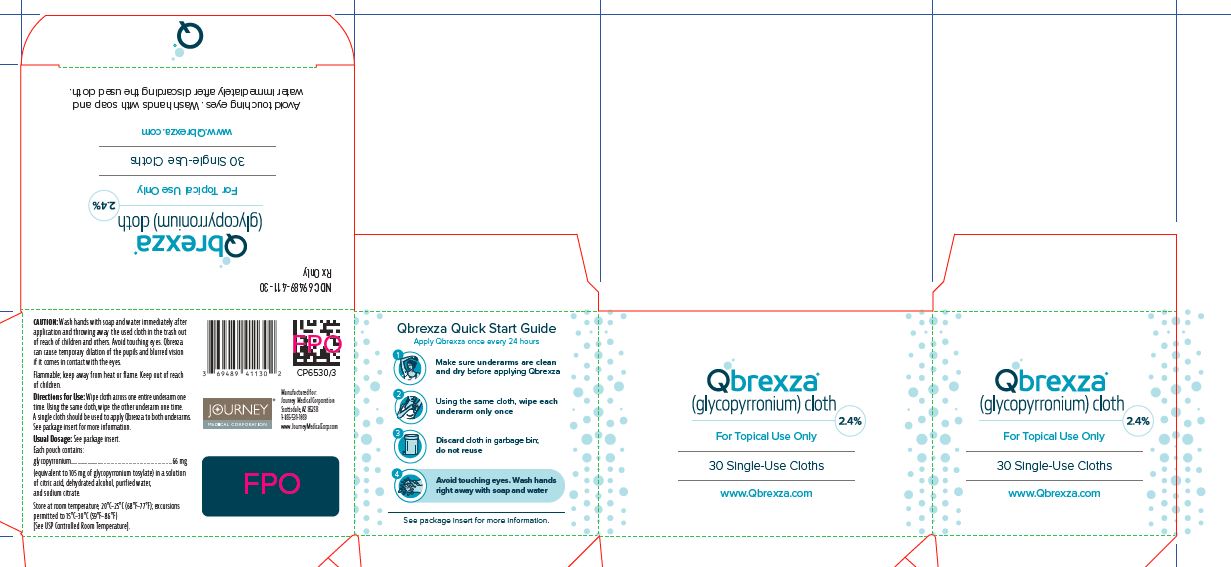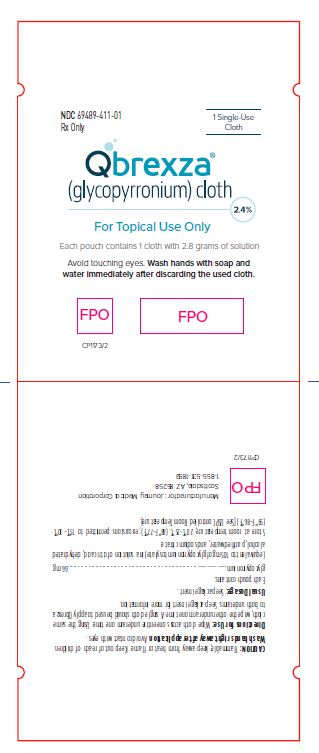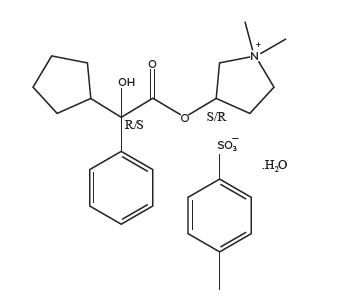 DRUG LABEL: Qbrexza
NDC: 69489-411 | Form: CLOTH
Manufacturer: Journey Medical Corporation
Category: prescription | Type: HUMAN PRESCRIPTION DRUG LABEL
Date: 20231219

ACTIVE INGREDIENTS: GLYCOPYRRONIUM TOSYLATE 2.4 g/100 g
INACTIVE INGREDIENTS: ANHYDROUS CITRIC ACID; TRISODIUM CITRATE DIHYDRATE; WATER; ALCOHOL

HIGHLIGHTS OF PRESCRIBING INFORMATION

These highlights do not include all the information needed to use QBREXZA® safely and effectively. See full prescribing information for QBREXZA.
QBREXZA (glycopyrronium) cloth, 2.4%, for topical use
Initial U.S. Approval: 2018

1 INDICATIONS AND USAGE

Qbrexza is an anticholinergic indicated for topical treatment of primary axillary hyperhidrosis in adults and pediatric patients 9 years of age and older (1).

2 DOSAGE AND ADMINISTRATION

For topical use only. Apply Qbrexza once daily to both axillae using a single cloth (2).

3 DOSAGE FORMS AND STRENGTHS

Cloth: A single-use cloth pre-moistened with 2.4% glycopyrronium solution (3).

4 CONTRAINDICATIONS

Qbrexza is contraindicated in patients with medical conditions that can be exacerbated by the anticholinergic effect of Qbrexza (e.g., glaucoma, paralytic ileus, unstable cardiovascular status in acute hemorrhage, severe ulcerative colitis, toxic megacolon complicating ulcerative colitis, myasthenia gravis, Sjogren’s syndrome) (4)

5 WARNINGS AND PRECAUTIONS

- New or worsening urinary retention: Use with caution in patients with a history of documented urinary retention (5.1).
- Control of body temperature: In the presence of high ambient temperature, heat illness may occur; avoid use if patients develop generalized lack of sweating when exposed to hot or very warm environmental temperatures (5.2).
- Operating machinery or an automobile: Transient blurred vision may occur with use of Qbrexza. If blurred vision occurs, discontinue use of Qbrexza until symptoms resolve; avoid operating a motor vehicle or other machinery until symptoms resolve (5.3).

6 ADVERSE REACTIONS

Most common adverse reactions (incidence ≥2%) are dry mouth, mydriasis, oropharyngeal pain, headache, urinary hesitation, vision blurred, nasal dryness, dry throat, dry eye, dry skin, constipation. Local skin reactions, including erythema, burning/stinging and pruritus were also common (>5%) (6.1).

To report SUSPECTED ADVERSE REACTIONS, contact Journey Medical Corp. at 1-855-531-1859 or FDA at 1-800-FDA-1088 or www.fda.gov/medwatch.

7 DRUG INTERACTIONS

Coadministration of Qbrexza with anticholinergic medications may result in additive interaction leading to an increase in anticholinergic adverse effects. Avoid coadministration of Qbrexza with other anticholinergic-containing drugs (7)

8 USE IN SPECIFIC POPULATIONS

- Pediatric use: Safety and efficacy are not established in patients under 9 years of age (8.4).

FULL PRESCRIBING INFORMATION

1 INDICATIONS AND USAGE

Qbrexza is indicated for topical treatment of primary axillary hyperhidrosis in adult and pediatric patients 9 years of age and older.

2 DOSAGE AND ADMINISTRATION

For topical use only.

Qbrexza is for topical use in the underarm area only and not for use in other body areas.

Qbrexza is administered by a single-use pre-moistened cloth packaged in individual pouches. Qbrexza should be applied to clean dry skin on the underarm areas only. Qbrexza should not be used more frequently than once every 24 hours.

Tear open the pouch and pull out the cloth, unfold the cloth, and wipe it across one entire underarm once. Using the same cloth, wipe the other underarm once. A single cloth should be used to apply Qbrexza to both underarms.

After applying Qbrexza, discard the cloth in the household trash out of reach of children and others. Wash hands immediately with soap and water after applying and discarding the Qbrexza cloth. Qbrexza may cause temporary dilation of the pupils and blurred vision if it comes in contact with the eyes. Avoid transfer of Qbrexza to the periocular area [see Warnings and Precautions (5.3)].

Do not apply Qbrexza to broken skin. Avoid using Qbrexza with occlusive dressings.

3 DOSAGE FORMS AND STRENGTHS

Cloth: A single-use cloth pre-moistened with 2.4% glycopyrronium solution

4 CONTRAINDICATIONS

Qbrexza is contraindicated in patients with medical conditions that can be exacerbated by the anticholinergic effect of Qbrexza (e.g., glaucoma, paralytic ileus, unstable cardiovascular status in acute hemorrhage, severe ulcerative colitis, toxic megacolon complicating ulcerative colitis, myasthenia gravis, Sjogren’s syndrome).

5 WARNINGS AND PRECAUTIONS

5.1 New or Worsening Urinary Retention

New or worsening signs and symptoms of urinary retention (e.g., difficulty passing urine, distended bladder) have occurred in patients taking Qbrexza with or without a history of documented urinary retention. Instruct patients to discontinue use immediately and consult a physician should any of these signs or symptoms develop.

Qbrexza should be used with caution in patients with prostatic hypertrophy or bladder-neck obstruction.

5.2 Control of Body Temperature

In the presence of high ambient temperature, heat illness (hyperpyrexia and heat stroke due to decreased sweating) can occur with the use of anticholinergic drugs such as Qbrexza. Advise patients using Qbrexza to watch for generalized lack of sweating when in hot or very warm environmental temperatures and to avoid use if not sweating under these conditions.

5.3 Operating Machinery or an Automobile

Transient blurred vision may occur with use of Qbrexza. If blurred vision occurs, the patient should discontinue use until symptoms resolve. Patients should be warned not to engage in activities that require clear vision such as operating a motor vehicle or other machinery, or performing hazardous work until the symptoms have resolved.

5.4 Risk of Accidental Exposure

Cases of accidental exposure resulting in mydriasis, anisocoria, and blurred vision have been reported in postmarketing surveillance of Qbrexza. The exposures occurred when children accessed Qbrexza wipes discarded in trash or when patients touched the periocular area after using Qbrexza. In most cases, the mydriasis, anisocoria, and blurred vision were temporary and resolved within one week following exposure. The risk of accidental exposure was increased in these cases by not adhering to recommendations for the appropriate use of Qbrexza.

Strict adherence to the recommended hand washing after use and disposal instructions is of the utmost importance to prevent accidental exposure. [see Dosage and Administration (2)].

6 ADVERSE REACTIONS

The following adverse reactions are described in greater detail in other sections

• New or Worsening Urinary Retention [see Warnings and Precautions (5.1)]

6.1 Clinical Trials Experience

Because clinical trials are conducted under widely varying conditions, adverse reaction rates observed in the clinical trials of a drug cannot be directly compared to rates in the clinical trials of another drug and may not reflect the rates observed in practice.

In two double-blind, vehicle-controlled clinical trials (Trial 1 [NCT02530281] and Trial 2 [NCT02530294]) of 459 subjects treated with Qbrexza once daily and 232 treated with vehicle, subjects were 9 to 76 years of age, 47% male, and the percentages of White, Black (including African Americans), and Asian subjects were 82%, 12%, and 1%, respectively.

Table 1 summarizes the most frequent adverse reactions (≥2%) in subjects with primary axillary hyperhidrosis treated with Qbrexza.

Table 1: Adverse Reactions Occurring in ≥2% of Subjects
Adverse Reactions | Qbrexza (N=459) n (%) | Vehicle (N=232) n (%)
Dry mouth | 111 (24.2%) | 13 (5.6%)
Mydriasis | 31 (6.8%) | 0
Oropharyngeal pain | 26 (5.7%) | 3 (1.3%)
Headache | 23 (5.0%) | 5 (2.2%)
Urinary hesitation | 16 (3.5%) | 0
Vision blurred | 16 (3.5%) | 0
Nasal dryness | 12 (2.6%) | 1 (0.4%)
Dry throat | 12 (2.6%) | 0
Dry eye | 11 (2.4%) | 1 (0.4%)
Dry skin | 10 (2.2%) | 0
Constipation | 9 (2.0%) | 0

Table 2 shows the most frequently reported local skin reactions, which were relatively common in both the Qbrexza and vehicle groups.

Table 2: Local Skin Reactions
Local Skin Reactions | Qbrexza (N=454)a n (%) | Vehicle (N=231)a n (%)
Erythema | 77 (17.0%) | 39 (16.9%)
Burning/stinging | 64 (14.1%) | 39 (16.9%)
Pruritus | 37 (8.1%) | 14 (6.1%)
a Patients with a post-baseline local skin reaction assessment

In an open-label safety trial (NCT02553798), 564 subjects were treated for up to an additional 44 weeks after completing Trial 1 or Trial 2. Adverse reactions occurring at a frequency ≥2.0% were: dry mouth (16.9%), vision blurred (6.7%), nasopharyngitis (5.8%), mydriasis (5.3%), urinary hesitation (4.2%), nasal dryness (3.6%), dry eye (2.9%), pharyngitis (2.2%), and application site reactions (pain [6.4%], dermatitis [3.8%], pruritus [3.8%], rash [3.8%], erythema [2.4%]).

6.2 Postmarketing Experience

The following adverse reactions have been identified during post-approval use of Qbrexza. Because the reactions are reported voluntarily from a population of uncertain size, it is not always possible to reliably estimate their frequency or establish a causal relationship to Qbrexza exposure.

• Genitourinary system disorders: new onset urinary retention [see Warnings and Precautions (5.1)]

7 DRUG INTERACTIONS

7.1 Anticholinergics

Coadministration of Qbrexza with anticholinergic medications may result in additive interaction leading to an increase in anticholinergic adverse effects [see Warnings and Precautions (5) and Adverse Reactions (6)]. Avoid coadministration of Qbrexza with other anticholinergic-containing drugs.

8 USE IN SPECIFIC POPULATIONS

8.1 Pregnancy

Risk Summary

There are no available data on Qbrexza use in pregnant women to inform a drug-associated risk for adverse developmental outcomes. In pregnant rats, daily oral administration of glycopyrrolate (glycopyrronium bromide) during organogenesis did not result in an increased incidence of gross external or visceral defects [see Data]. When glycopyrrolate was administered intravenously to pregnant rabbits during organogenesis, no adverse effects on embryo-fetal development were seen. The available data do not support relevant comparisons of systemic glycopyrronium exposures achieved in the animal studies to exposures observed in humans after topical use of Qbrexza.

The estimated background risks of major birth defects and miscarriage for the indicated population are unknown. In the U.S. general population, the estimated background risk of major birth defects and miscarriage in clinically recognized pregnancies is 2-4% and 15-20%, respectively.

Data

Animal Data

Glycopyrrolate was orally administered to pregnant rats at dosages of 50, 200, and 400 mg/kg/day during the period of organogenesis. Glycopyrrolate had no effect on maternal survival, but significantly reduced mean maternal body weight gain over the period of dosing at all dosages evaluated. Mean fetal weight was significantly reduced in the 200 and 400 mg/kg/day dose groups. There were two litters with all resorbed fetuses in the 400 mg/kg/day dose group. There were no effects of treatment on the incidence of gross external or visceral defects. Minor treatment-related skeletal effects included reduced ossification of various bones in the 200 and 400 mg/kg/day dose groups; these skeletal effects were likely secondary to maternal toxicity.

Glycopyrrolate was intravenously administered to pregnant rabbits at dosages of 0.1, 0.5, and 1.0 mg/kg/day during the period of organogenesis. Glycopyrrolate did not affect maternal survival under the conditions of this study. Mean maternal body weight gain and mean food consumption over the period of dosing were lower than the corresponding control value in the 0.5 and 1.0 mg/kg/day treatment groups. There were no effects of treatment on fetal parameters, including fetal survival, mean fetal weight, and the incidence of external, visceral, or skeletal defects.

Female rats that were pregnant or nursing were orally dosed with glycopyrrolate daily at dosages of 0, 50, 200, or 400 mg/kg/day, beginning on day 7 of gestation, and continuing until day 20 of lactation. Mean body weight of pups in all treatment groups was reduced compared to the control group during the period of nursing, but eventually recovered to be comparable to the control group, post-weaning. No other notable delivery or litter parameters were affected by treatment in any group, including no effects on mean duration of gestation or mean numbers of live pups per litter. No treatment-related effects on survival or adverse clinical signs were observed in pups. There were no effects of maternal treatment on behavior, learning, memory, or reproductive function of pups.

8.2 Lactation

Risk Summary

There are no data on the presence of glycopyrrolate or its metabolites in human milk, the effects on the breastfed infant, or the effects on milk production. The developmental and health benefits of breastfeeding should be considered along with the mother’s clinical need for Qbrexza and any potential adverse effects on the breastfed infant from Qbrexza or from the underlying maternal condition.

8.4 Pediatric Use

The safety, effectiveness and pharmacokinetics of Qbrexza have been established in pediatric patients age 9 years and older for topical treatment of primary axillary hyperhidrosis [see Clinical Pharmacology (12.3)]. Use of Qbrexza in this age group is supported by evidence from two multicenter, randomized, double-blind, parallel-group, vehicle-controlled 4-week trials which included 34 pediatric subjects 9 years and older [see Adverse Reactions (6.1) and Clinical Studies (14)]. The safety and effectiveness of Qbrexza have not been established in pediatric patients under 9 years of age.

8.5 Geriatric Use

Clinical trials of Qbrexza did not include sufficient numbers of subjects age 65 years and older to determine whether they respond differently from younger subjects.

8.6 Renal Impairment

The elimination of glycopyrronium is severely impaired in patients with renal failure [see Clinical Pharmacology (12.3)].

10 OVERDOSAGE

Because glycopyrronium is a quaternary amine which does not easily cross the blood-brain barrier, symptoms of glycopyrronium overdosage are generally more peripheral in nature rather than central compared to other anticholinergic agents. Associated signs and symptoms related to excessive anticholinergic activity may include flushing, hyperthermia, tachycardia, ileus, urinary retention, loss of ocular accommodation and light sensitivity due to mydriasis.

In the case of overdose when symptoms are severe or life threatening, therapy may include:

- Managing per standard of care any acute conditions such as hyperthermia, coma, and/or seizures, as applicable, and managing any myoclonic or choreoathetoid movements which may lead to rhabdomyolysis in some cases of anticholinergic overdosage
- Managing severe urinary retention with catheterization if not spontaneously reversed within several hours
- Providing cardiovascular support and/or controlling arrhythmias
- Maintaining an open airway, providing ventilation as necessary
- Administering a quaternary ammonium anticholinesterase such as neostigmine to help alleviate severe and/or life threatening peripheral anticholinergic effects.

Topical overdosing of Qbrexza could result in an increased incidence or severity of local skin reactions. Administration of Qbrexza under occlusive conditions may result in an increase in anticholinergic effects, including dry mouth and urinary hesitation.

11 DESCRIPTION

Qbrexza (glycopyrronium) cloth, 2.4% is an anticholinergic drug available as a clear, colorless to pale yellow solution on a single-use pre-moistened cloth (an absorbent polypropylene pad) packaged in a pouch for topical administration. Each pouch contains 105 mg glycopyrronium tosylate, equivalent to 66 mg of glycopyrronium. The inactive ingredients are citric acid, dehydrated alcohol, purified water, and sodium citrate.

Glycopyrronium tosylate is chemically described as pyrrolidinium, 3-[(2-cyclopentyl-2-hydroxy-2-phenylacetyl)oxy]-1,1-dimethyl-, 4-methylbenzensulfonate, hydrate (1:1:1) with an empirical formula of C26H37NO7S and a molecular weight of 507.6. The structural formula is represented below:

12 CLINICAL PHARMACOLOGY

12.1 Mechanism of Action

Glycopyrronium is a competitive inhibitor of acetylcholine receptors that are located on certain peripheral tissues, including sweat glands. In hyperhidrosis, glycopyrronium inhibits the action of acetylcholine on sweat glands, reducing sweating.

12.2 Pharmacodynamics

The pharmacodynamics of Qbrexza are not known.

12.3 Pharmacokinetics

Absorption

The pharmacokinetics of glycopyrronium were evaluated in adult and pediatric patients with primary axillary hyperhidrosis following Qbrexza once daily applied to the axillae for 5 days. The mean ± SD exposures of glycopyrronium are presented in Tables 3 and 4. There was no evidence of accumulation.

Table 3: Mean ± SD Plasma Exposures of Glycopyrronium in Adults Following Qbrexza Once Daily for 5 days
Parameter | Adult Patients
Cmax (ng/mL) | 0.08 ± 0.04
AUC0-6h (h∗ng/mL) | 0.2 ± 0.14
AUC0-24h (h∗ng/mL) | 0.88 ± 0.57
Median Tmax (Range) (h) | 1 (0, 10)
Abbreviations: Maximum concentration (Cmax), Area under the time concentration curve
(AUC) between 0 and 6 hours following administration of Qbrexza (AU0-6h), AUC between
0 and 24 hours following administration of Qbrexza (AUC0-24h)

Distribution

After IV administration, glycopyrronium has a mean volume of distribution in children aged 1 to 14 years of approximately 1.3 to 1.8 L/kg, with a range from 0.7 to 3.9 L/kg. In adults aged 60-75 years, the volume of distribution was lower (0.42 L/kg ± 0.22).

Elimination

Metabolism

A small proportion of glycopyrronium is metabolized following IV administration. The metabolic pathway for glycopyrronium is not characterized.

Excretion

Following administration of a single radiolabeled IV glycopyrronium dose to adult subjects who underwent surgery for cholelithiasis, approximately 85% of total radioactivity was excreted in urine and < 5% was present in bile drainage. Greater than 80% of the radioactivity in both urine and bile was unchanged drug.

Specific Populations

The pharmacokinetics of glycopyrronium were not evaluated in pregnant women or patients with hepatic impairment.

Pediatric Subjects

The mean ± SD exposures of glycopyrronium in pediatric subjects following Qbrexza once daily for 5 days are presented in Table 4. There was no evidence of accumulation.

Table 4: Mean ± SD Plasma Exposures of Glycopyrronium in Pediatric Subjects Aged 10 to 17 years Following Qbrexza Once Daily for 5 days
Parameter | Pediatric Patients
Cmax (ng/mL) | 0.07 ± 0.06
AUC0-6h (h∗ng/mL) | 0.18 ± 0.13
AUC0-24h (h∗ng/mL) | Not calculated
Median Tmax (Range) (h) | 1.5 (0, 6)

Patients with Renal Impairment

Following a 4 mcg/kg IV dose of a glycopyrronium formulation for IV use, mean glycopyrronium AUC (10.6 mcg·h/L), CL (0.43 L/h/kg) and 3-hour urinary excretion (0.7%) were significantly different in uremic subjects undergoing renal transplantation surgery than those of healthy subjects (3.73 mcg·h/L, 1.14 L/h/kg, and 50%, respectively).

Pharmacokinetics of Qbrexza in subjects with renal impairment has not been studied.

In Vitro Studies

In vitro studies indicated that under the conditions of clinical use, Qbrexza is not expected to induce cytochrome P450 (CYP) enzymes 1A2, 2B6 and 3A4; or inhibit 1A2, 2B6, 2C8, 2C9, 2C19, 2D6 and 3A4.

13 NONCLINICAL TOXICOLOGY

13.1 Carcinogenesis, Mutagenesis, Impairment of Fertility

Glycopyrronium tosylate was not carcinogenic when topically applied to rats daily for up to 24 months in solution at concentrations of 1%, 2%, and 4% w/w.

When glycopyrrolate was administered via oral gavage to mice for up to 24 months at dosages of 2.5, 7, and 20 mg/kg/day in both genders, no significant changes in tumor incidence were observed when compared to control.

When glycopyrrolate was administered via oral gavage to rats for up to 24 months at dosages of 5, 15, and 40 mg/kg/day in both genders, no significant changes in tumor incidence were observed when compared to control.

Glycopyrrolate was negative in a battery of genetic toxicology studies that included a bacterial reverse mutation (Ames) assay, a mouse lymphoma assay conducted with L5178Y/TK+/- cells, and an in vivo micronucleus assay with mice. Glycopyrronium tosylate was negative in an Ames assay.

Glycopyrrolate was assessed for effects on fertility or general reproductive function in rats. Rats of both genders received glycopyrrolate at dosages up to 100 mg/kg/day via oral gavage. No treatment-related effects on fertility or reproductive parameters were observed in either gender.

14 CLINICAL STUDIES

14.1 Efficacy and Safety Trials

Two randomized, vehicle-controlled multicenter trials, Trial 1 (NCT02530281) and Trial 2 (NCT02530294), were conducted in subjects with primary axillary hyperhidrosis and enrolled a total of 697 subjects 9 years of age or older. Inclusion criteria required that prior to the start of treatment, all subjects produce at least 50 mg of sweat in each axilla over a 5-minute period and rate the severity of their sweating daily over a week with a mean score of 4 or higher on the ASDD item #2, a patient reported outcome instrument scored from 0 (no sweating) to 10 (worst possible sweating). The median sweat production over 5 minutes at baseline was 122 mg in the Qbrexza arm and 113 mg in the vehicle arm in Trial 1, and 127 mg in the Qbrexza arm and 117 mg in the vehicle arm in Trial 2. The average weekly mean score on the ASDD item #2 at baseline was approximately 7.2 across both trials.

Subjects were randomized to receive either Qbrexza or vehicle applied once daily to each axilla. The co-primary endpoints were the proportion of subjects having at least a 4-point improvement from baseline in the weekly mean ASDD item #2 score at Week 4 and the mean absolute change from baseline in gravimetrically measured sweat production at Week 4.

Clinical Response

The results of Trial 1 and Trial 2 are presented in Table 5 below.

Table 5: Primary Efficacy Outcomes in Subjects with Primary Axillary Hyperhidrosis
 | Trial 1 |  | Trial 2
 | Qbrexza, 2.4% N = 229 | Vehicle N = 115 | Qbrexza 2.4% N = 234 | Vehicle N = 119
ASDD Item #2 Response at Week 4:
Proportion of subjects with at least a 4-point improvement from baseline in the weekly mean ASDD item #2 at Week 4 | 53% | 28% | 66% | 27%
Change from Baseline in Sweat Production at Week 4 (mg/5 minutes):
Median | -81 | -66 | -79 | -58
25th percentile, 75th percentile | -149, -40 | -106, -28 | -144, -45 | -122, -21

16 HOW SUPPLIED/STORAGE AND HANDLING

16.1 How Supplied

Qbrexza is supplied as:

A single-use cloth pre-moistened with a 2.4% glycopyrronium solution in a pouch

Carton of 30 pouches NDC 69489-411-30

16.2 Storage and Handling

Store at room temperature 20° - 25°C (68° - 77°F); excursions permitted to 15° - 30°C (59° - 86°F) [See USP Controlled Room Temperature].

Qbrexza is flammable; keep away from heat or flame.

17 PATIENT COUNSELING INFORMATION

Advise the patient to read the FDA-approved patient labeling (Patient Information).

New or Worsening Urinary Retention

Instruct patients to be alert for signs and symptoms of urinary retention (e.g., difficulty passing urine, distended bladder). Instruct patients to discontinue use and consult a physician immediately should any of these signs or symptoms develop.

Control of Body Temperature (Risk of Overheating or Heat Illness)

In the presence of high ambient temperature, heat illness due to decreased sweating can occur with the use of anticholinergic drugs such as Qbrexza. Advise patients using Qbrexza to watch for generalized lack of sweating when in hot or very warm environmental temperatures and to avoid use if not sweating under these conditions.

Operating Machinery or an Automobile

Transient blurred vision may occur with Qbrexza. If this occurs, instruct patients to contact their healthcare provider, discontinue use of Qbrexza and avoid operating a motor vehicle or other machinery, or performing hazardous work until symptoms resolve.

Instructions for Administering Qbrexza

It is important for patients to understand how to correctly apply Qbrexza (see Patient Information).

- Instruct patients to use one cloth to apply Qbrexza to both axillae by wiping the cloth across one underarm, ONE TIME.
- Using the same cloth, apply the medication to the other underarm, ONE TIME.
- After applying Qbrexza, discard the cloth in the household trash out of reach of children and others.
- Wash your hands with soap and water right away after you apply Qbrexza and have thrown away the cloth.
- Inform patients to avoid touching the periocular area. The Qbrexza that is still on your hands can cause you to have temporary pupil dilation and blurred vision if you touch your eyes.
- Remind patients not to apply Qbrexza to other body areas or to broken skin. Instruct patients to avoid using Qbrexza with occlusive dressings.
- Qbrexza is flammable; avoid use near heat or flame.

Manufactured for:

Journey Medical Corporation
Scottsdale, AZ 85258

Version 2, October 2022

PATIENT INFORMATION

Qbrexza™ (kew brex’ zah)
(glycopyrronium)
cloth, 2.4%

Important Information: Qbrexza is for use on the skin in the underarm area only.

What is Qbrexza?

Qbrexza is a prescription anticholinergic medicine used on the skin (topical) to treat excessive underarm sweating (primary axillary hyperhidrosis) in adults and children 9 years of age and older.

It is not known if Qbrexza is safe and effective in children under 9 years of age.

Who should not use Qbrexza?

Do not use Qbrexza if you have certain medical conditions that can be made worse by taking an anticholinergic medicine such as glaucoma, severe ulcerative colitis or certain other serious bowel problems associated with severe ulcerative colitis, myasthenia gravis, and Sjogren’s syndrome.

Talk to your healthcare provider if you are not sure if you have a medical condition that can be made worse by taking an anticholinergic medicine.

Before using Qbrexza, tell your healthcare provider about all of your medical conditions, including if you:

- have prostate or bladder problems, or problems passing urine
- have kidney problems
- are pregnant or plan to become pregnant. It is not known if Qbrexza will harm your unborn baby.
- are breastfeeding or plan to breastfeed. It is not known if Qbrexza passes into your breast milk. Talk to your healthcare provider about the best way to feed your baby during treatment with Qbrexza.

Tell your healthcare provider about all the medicines you take, including prescription medicines, over-the-counter medicines, vitamins, and herbal supplements.

Qbrexza may affect the way other medicines work causing side effects. Especially tell your healthcare provider if you take anticholinergic medicines.

Know the medicines you take. Keep a list of your medicines with you and show it to your healthcare provider and pharmacist when you get a new medicine.

How should I use Qbrexza?

- Use Qbrexza exactly as your healthcare provider tells you to use it.
- Qbrexza comes as a single-use pre-moistened cloth in individual pouches.
- Qbrexza should be applied to the clean, dry, intact skin, of your underarm areas only. Do not apply Qbrexza to broken skin. Do not cover the treated area with a plastic (occlusive) dressing.
- Apply Qbrexza to both underarm areas using 1 cloth 1 time every 24 hours.

Applying Qbrexza:

- Carefully tear open the pouch to avoid tearing the Qbrexza cloth.
- Unfold the Qbrexza cloth and apply Qbrexza by wiping across 1 entire underarm 1 time. Using the same Qbrexza cloth, wipe across the other underarm 1 time.
- Throw away (discard) the used Qbrexza cloth in the trash out of the reach of children and others.
- Wash your hands right away after you apply Qbrexza and have thrown away the cloth. It is important that you wash your hands because the Qbrexza that is still on your hands can cause you to have blurred vision if you touch your eyes.
- Do not reuse the Qbrexza cloth.

What should I avoid while using Qbrexza?

- • Avoid touching eyes. Qbrexza may cause you to have blurred vision that is temporary. If you develop blurred vision, call your healthcare provider, stop using Qbrexza and do not drive, operate machinery, or do hazardous work until your vision is clear.
- Qbrexza is flammable. Avoid heat and flame while applying Qbrexza to your skin

What are the possible side effects of Qbrexza?

Qbrexza can cause serious side effects, including:

- New or worsened urinary retention.People who use Qbrexza may develop new or worse urinary retention. Urinary retention can be caused by a blockage in your bladder. Urinary retention can also happen in men who have a larger than normal prostate. Symptoms of urinary retention may include:
  - difficulty urinating
  - urinating frequently
  - urination in a weak stream or drips
  - full bladder or difficulty emptying your bladder (distended bladder)
    If you have these symptoms, stop using Qbrexza and call your healthcare provider right away.
- Problems with control of your body temperature. Qbrexza can cause you to have decreased sweating in areas other than the underarm area which could cause you to become overheated and to develop heat illness. When in hot or very warm temperatures, watch for lack of sweating on your body (generalized) and stop using Qbrexza if you develop lack of sweating on your body.
  Stop using Qbrexza and call your healthcare provider right away if you develop any of these symptoms of heat illness:
  - hot, red skin
  - decreased alertness or passing out (unconsciousness)
  - fast, weak pulse
  - fast, shallow breathing
  - increased body temperature (fever)
- Blurred vision. If you develop blurred vision during treatment with Qbrexza, call your healthcare provider, stop using Qbrexza and do not drive, or operate machinery, or do hazardous work until your vision is clear.

- The most common side effects of Qbrexza include:
  - dry mouth
  - dilation of the pupils of your eyes (mydriasis)
  - sore throat
  - skin redness, burning/stinging or itching in underarm area
  - headache
  - problems with urination
  - blurred vision
  - nasal dryness
  - throat, eye, and skin dryness
  - constipation

These are not all of the possible side effects of Qbrexza.

Call your doctor for medical advice about side effects. You may report side effects to FDA at 1-800-FDA-1088.

How should I store Qbrexza?

- Store Qbrexza at room temperature between 68°F and 77°F (20°C and 25°C).
- Qbrexza is flammable. Keep Qbrexza away from heat and flame.

Keep Qbrexza and all medicines out of the reach of children.

General information about the safe and effective use of Qbrexza.

Medicines are sometimes prescribed for purposes other than those listed in a Patient Information leaflet. Do not use Qbrexza for a condition for which it was not prescribed. Do not give Qbrexza to other people, even if they have the same symptoms you have. It may harm them. You can ask your pharmacist or healthcare provider for information about Qbrexza that is written for health professionals.

What are the ingredients in Qbrexza?

Active Ingredient: glycopyrronium tosylate

Inactive Ingredients: citric acid, dehydrated alcohol, purified water, and sodium citrate

Manufactured for: Journey Medical Corporation, Scottsdale, AZ 85258

For more information, go to www.Qbrexza.com or call 1-855-531-1859.

This Patient Information has been approved by the U.S. Food and Drug Administration.

Revised: 10/2022

PRINCIPAL DISPLAY PANEL - NDC: 69489-411-01 - 1-Count Pouch Label

NDC 69489-411-01
Rx Only 1 Single-use

Cloth

Qbrexza®
(glycopyrronium) cloth
2.4%

For Topical Use Only

Each pouch contains 1 cloth with 2.8 grams of solution

Avoid touching eyes. Wash hands with soap and water

immediately after discarding the used cloth.

PRINCIPAL DISPLAY PANEL - NDC: 69489-411-30 - 30-Count Carton Label

NDC 69489-411-30

Rx Only

Qbrexza®
(glycopyrronium) cloth
2.4%

For Topical Use Only

30 Single-use Cloths

www.Qbrexza.com

Avoid touching eyes. Wash hands with soap and water

immediately after discarding the used cloth.